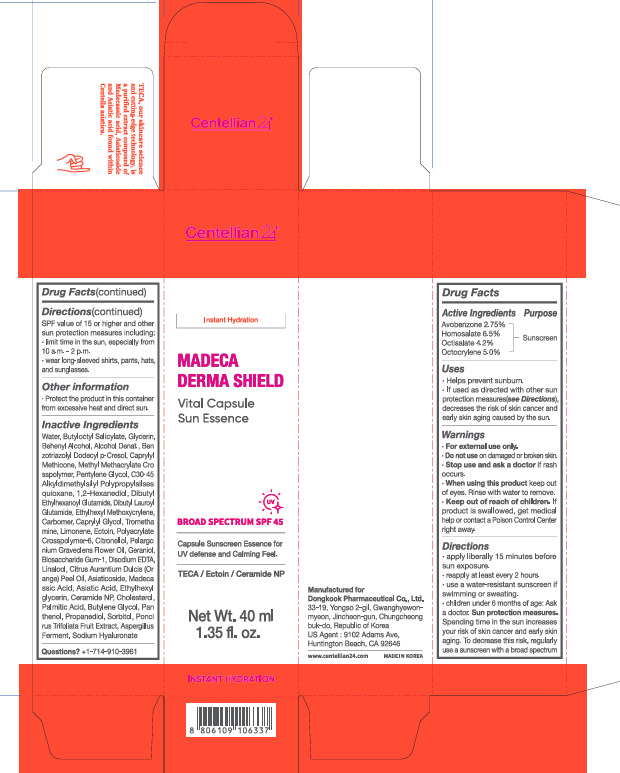 DRUG LABEL: Centellian24 Madeca Derma Shield Vital Sun Essence
NDC: 70541-128 | Form: CREAM
Manufacturer: 70541
Category: otc | Type: HUMAN OTC DRUG LABEL
Date: 20251201

ACTIVE INGREDIENTS: AVOBENZONE 2.75 g/100 mL; OCTOCRYLENE 5 g/100 mL; HOMOSALATE 6.5 g/100 mL; OCTISALATE 4.2 g/100 mL
INACTIVE INGREDIENTS: WATER

Dosage and adminstration

Directions
· apply liberally 15 minutes before sun exposure.
· reapply at least every 2 hours.
· use a water-resistant sunscreen if swimming or sweating.
· children under 6 months of age: Ask a doctor. Sun protection measures. Spending time in the sun increases your risk of skin cancer and early skin aging. To decrease this risk, regularly use a sunscreen with a broad spectrum SPF value of 15 or higher and other sun protection measures including:
· limit time in the sun, especially from 10 a.m. – 2 p.m.
· wear long-sleeved shirts, pants, hats, and sunglasses.

Warnings

· For external use only.
· Do not use on damaged or broken skin.
· Stop use and ask a doctor if rash occurs.
· When using this product keep out of eyes. Rinse with water to remove.
· Keep out of reach of children. If product is swallowed, get medical help or contact a Poison Control Center right away.

INACTIVE INGREDIENT

Inactive Ingredients
Water, Butyloctyl Salicylate, Glycerin, Behenyl Alcohol, Alcohol Denat., Benzotriazolyl Dodecyl p-Cresol, Caprylyl Methicone, Methyl Methacrylate Crosspolymer, Pentylene Glycol, C30-45 Alkyldimethylsilyl Polypropylsilsesquioxane, 1,2-Hexanediol, Dibutyl Ethylhexanoyl Glutamide, Dibutyl Lauroyl Glutamide, Ethylhexyl Methoxycrylene, Carbomer, Caprylyl Glycol, Tromethamine, Limonene, Ectoin, Polyacrylate Crosspolymer-6, Citronellol, Pelargonium Graveolens Flower Oil, Geraniol, Biosaccharide Gum-1, Disodium EDTA, Linalool, Citrus Aurantium Dulcis (Orange) Peel Oil, Asiaticoside, Madecassic Acid, Asiatic Acid, Ethylhexylglycerin, Ceramide NP, Cholesterol, Palmitic Acid, Butylene Glycol, Panthenol, Propanediol, Sorbitol, Poncirrus Trifoliata Fruit Extract, Aspergillus Ferment, Sodium Hyaluronate

Uses

Uses · Helps prevent sunburn. · If used as directed with other sun protection measures (see Directions), decreases the risk of skin cancer and early skin aging caused by the sun.

Purpose

Sunscreen

Keep out of reach of children. If product is swallowed, get medical help or contact a Poison Control Center right away.